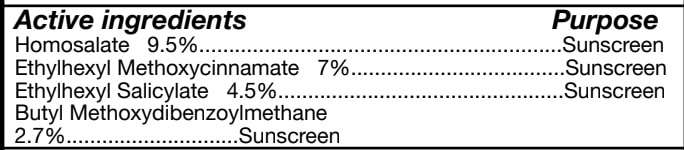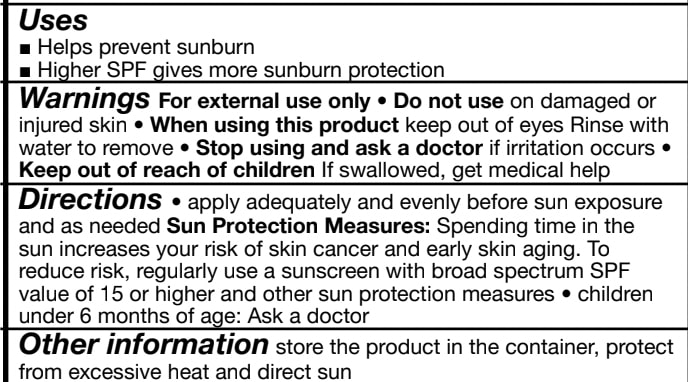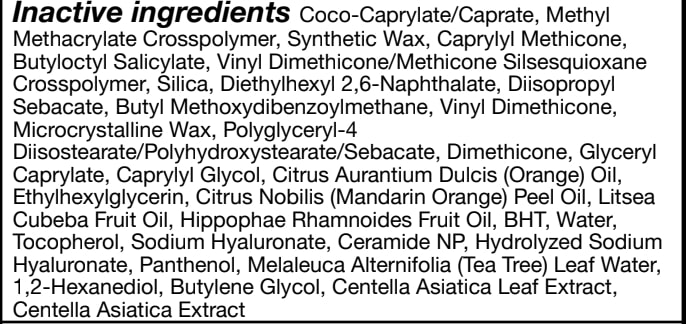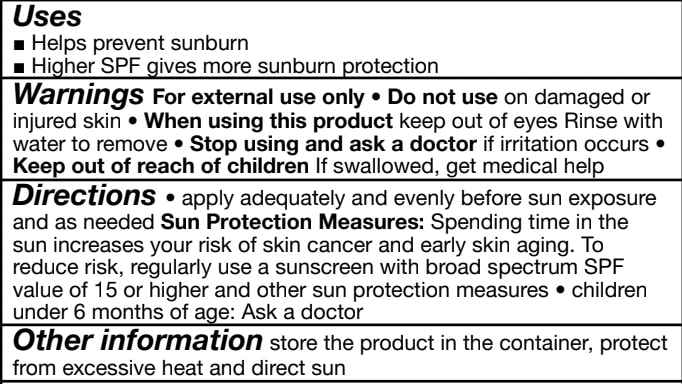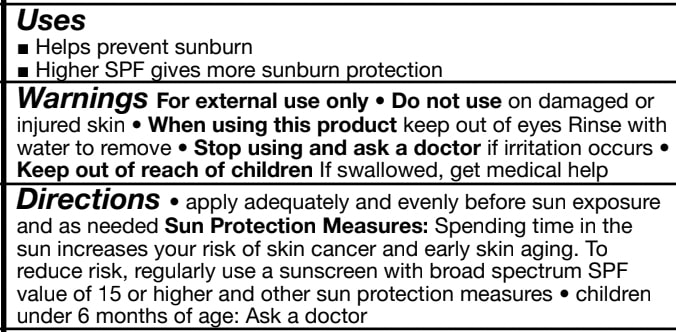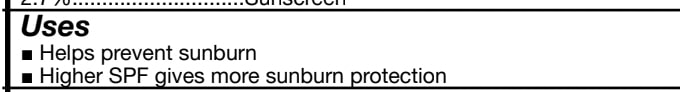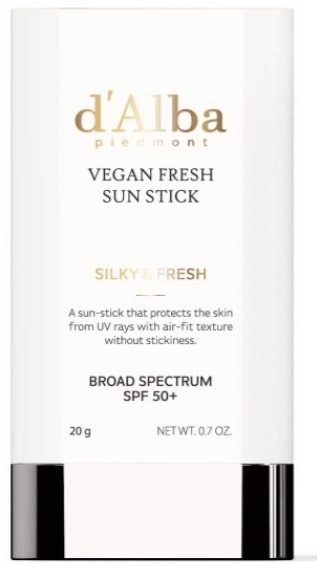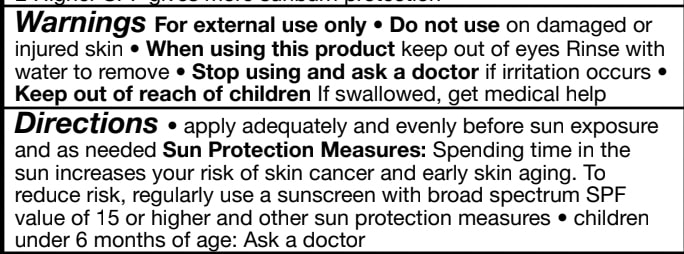 DRUG LABEL: dAlba Vegan Fresh Sun Stick
NDC: 84662-050 | Form: CREAM
Manufacturer: ADMTMAX LLC
Category: otc | Type: HUMAN OTC DRUG LABEL
Date: 20250608

ACTIVE INGREDIENTS: HOMOSALATE 9.5 mg/19 g
INACTIVE INGREDIENTS: COCO-CAPRYLATE/CAPRATE

d'Alba Vegan Fresh Sun Stick